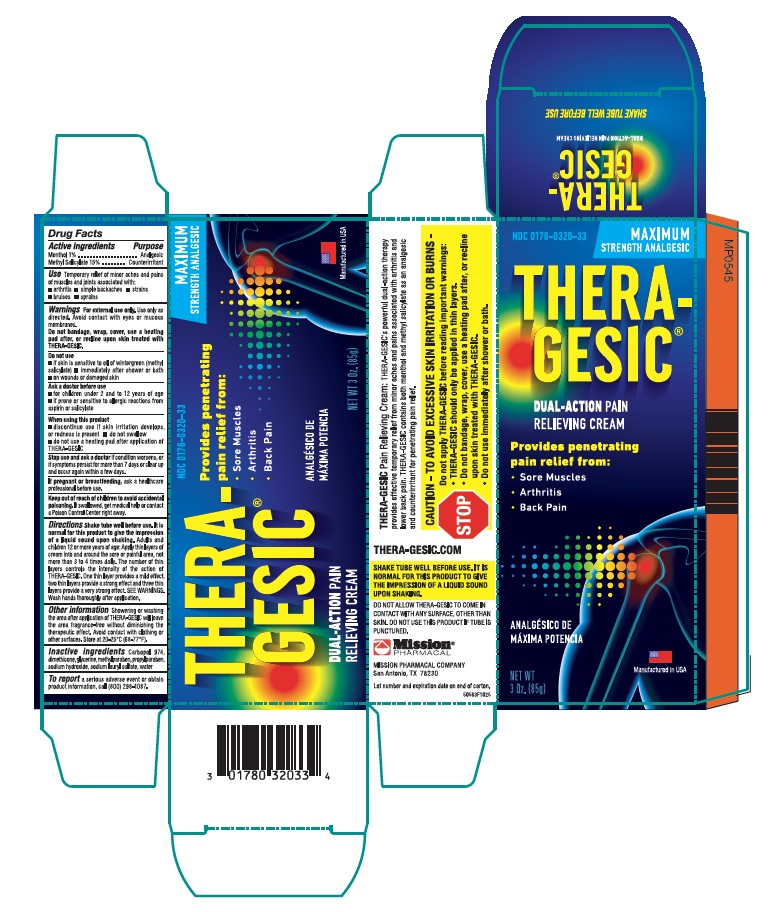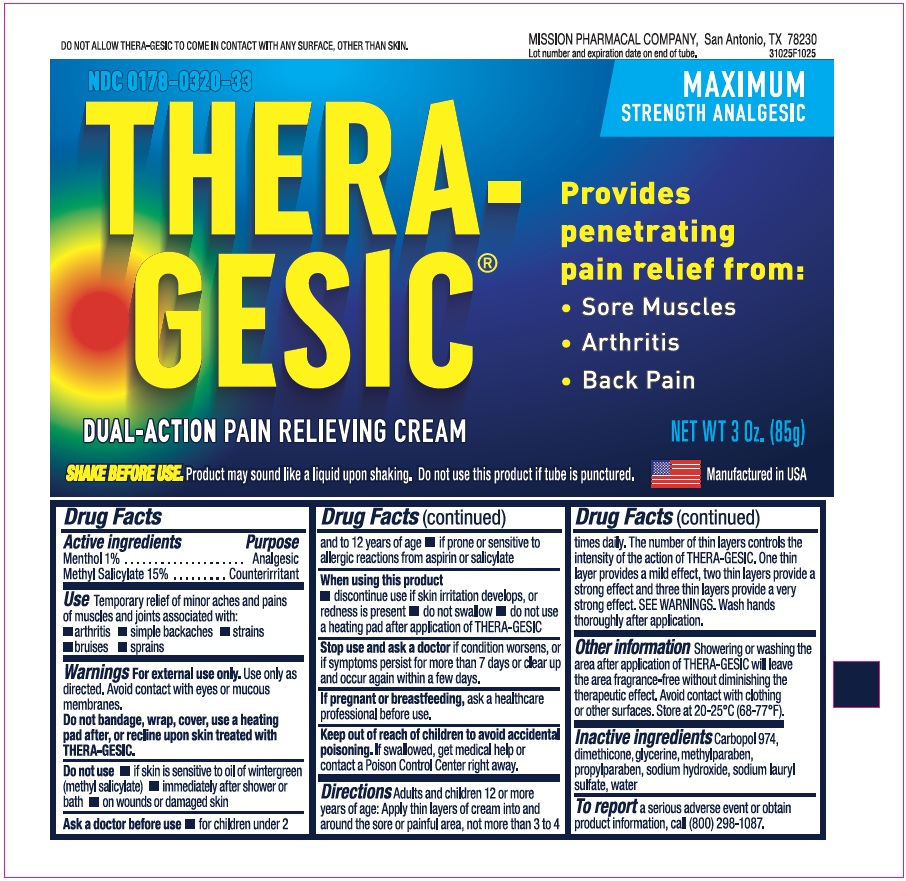 DRUG LABEL: Theragesic
NDC: 0178-0320 | Form: CREAM
Manufacturer: Mission Pharmacal Company
Category: otc | Type: HUMAN OTC DRUG LABEL
Date: 20251217

ACTIVE INGREDIENTS: METHYL SALICYLATE 150 mg/1 g; MENTHOL 10 mg/1 g
INACTIVE INGREDIENTS: WATER; DIMETHICONE; GLYCERIN; CARBOMER 934; TROLAMINE; METHYLPARABEN; SODIUM LAURYL SULFATE; PROPYLPARABEN

THERA-GESIC®Creme

Drug Facts

Active Ingredients

Purpose

Menthol 1%............................................................................................................................................................................................................................................................................................................................................................................... Analgesic

Methyl Salicylate 15%......................................................................................................................................................................................................................................................................................................................................................... Counterirritant

Use

temporary relief of minor aches and pains of muscles and joints associated with:

- arthritis
- simple backaches
- strains
- bruises
- sprains

Warnings

For external use only.Use only as directed. Avoid contact with eyes or mucous membranes.

Do not bandage, wrap, cover, use a heating pad after, or recline upon skin treated with THERA-GESIC®.

Do not use

- immediately shower or bath
- if skin is sensitive to oil of wintergreen (methyl salicylate)
- on wounds or damaged skin

Ask a doctor before use

- for children under 2 and to 12 years of age
- if prone or sensitive to allergic reaction from aspirin or salicylate

When using this product

- discontinue use if skin irritation develops, or redness is present
- do not swallow
- do not use a heating pad after application of THERA-GESIC®

Stop use and ask a doctor ifcondition worsens, or if symptoms persist for more than 7 days or clear up and occur again within a few days.

PREGNANCY OR BREAST FEEDING

If pregnant or breast-feeding,ask a health professional before use.

Keep out of reach of children to avoid accidental poisoning.If swallowed, get medical help or contact a Poison Control Center right away.

Directions

Adults and children 12 or more years of age. Apply thin layers of crème into and around the sore or painful area, not more than 3 to 4 times daily. The number of thin layers controls the intensity of the action of THERA-GESIC®. One this layer provides a mild effect, two thin layers provide a strong effect and three thin layers provide a very strong effect. SEE WARNINGS. Wash hands thoroughly after application.

Other information

Showering or washing the area after application of THERA-GESIC®will leave the area fragrance-free without diminishing the therapeutic effect. Avoid contact with clothing or other surfaces. Store at 20-25°C (68-77°F).

Inactive ingredients

QUESTIONS

Questions(210) 696-8400 (M-Th 8:00-5:30 CST)

PRECAUTIONS

SHARE BEFORE USE: IT IS NORMAL FOR THIS PRODUCT TO GIVE THE IMPRESSION OF A LIQUID SOUND UON SHAKING. DO NOT ALLOW THERA-GESIC®TO COMEIN CONTACT WITH ANY SURFACE, OTHER THAN SKIN.

Do not use this product if tube is punctured. Lot number and expiration date on end of carton.

MISSION PHARMACAL COMPANY, San Antonio, TX 78230 1355

50588 03 Rev 001090